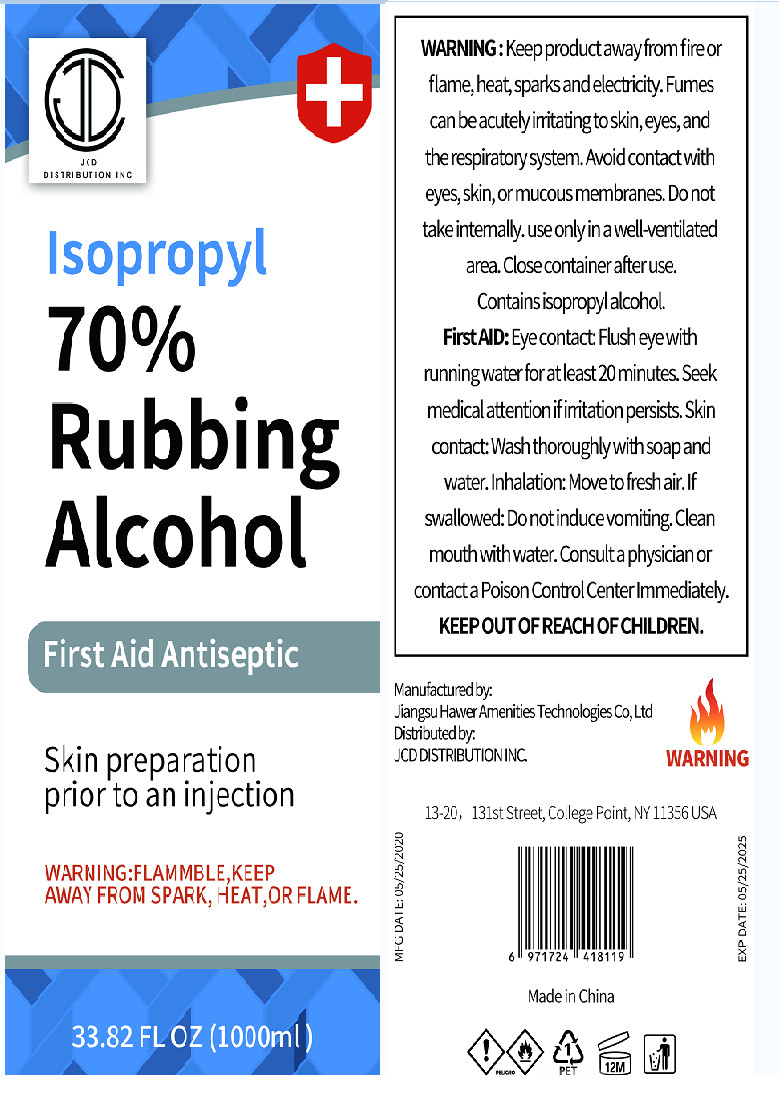 DRUG LABEL: Isopropyl Rubbing Alcohol 70%
NDC: 41254-009 | Form: LIQUID
Manufacturer: Jiangsu Hawer Amenities Technology Co.,Ltd
Category: otc | Type: HUMAN OTC DRUG LABEL
Date: 20200611

ACTIVE INGREDIENTS: ISOPROPYL ALCOHOL 750 mL/1000 mL
INACTIVE INGREDIENTS: WATER

DOSAGE AND ADMINISTRATION

Store in a cool and dry place

INACTIVE INGREDIENT

Aqua

INDICATIONS AND USAGE

Take a small amount of product on the surface of the object until dry

ACTIVE INGREDIENT

isopropyl alcohol

keep out of reach of children

PURPOSE

Disinfection
Sterilization

WARNINGS

Keep product away from fire or flame,heat, sparks and electricity.Fumes can be acutely initating to skin,eyes, and the respiratory system. Avoid contact with eyes, skin,or mucous membranes. Do not take intermally. use only in a well-verntilated area. Close container after use.Contains isopropyl alcchol.